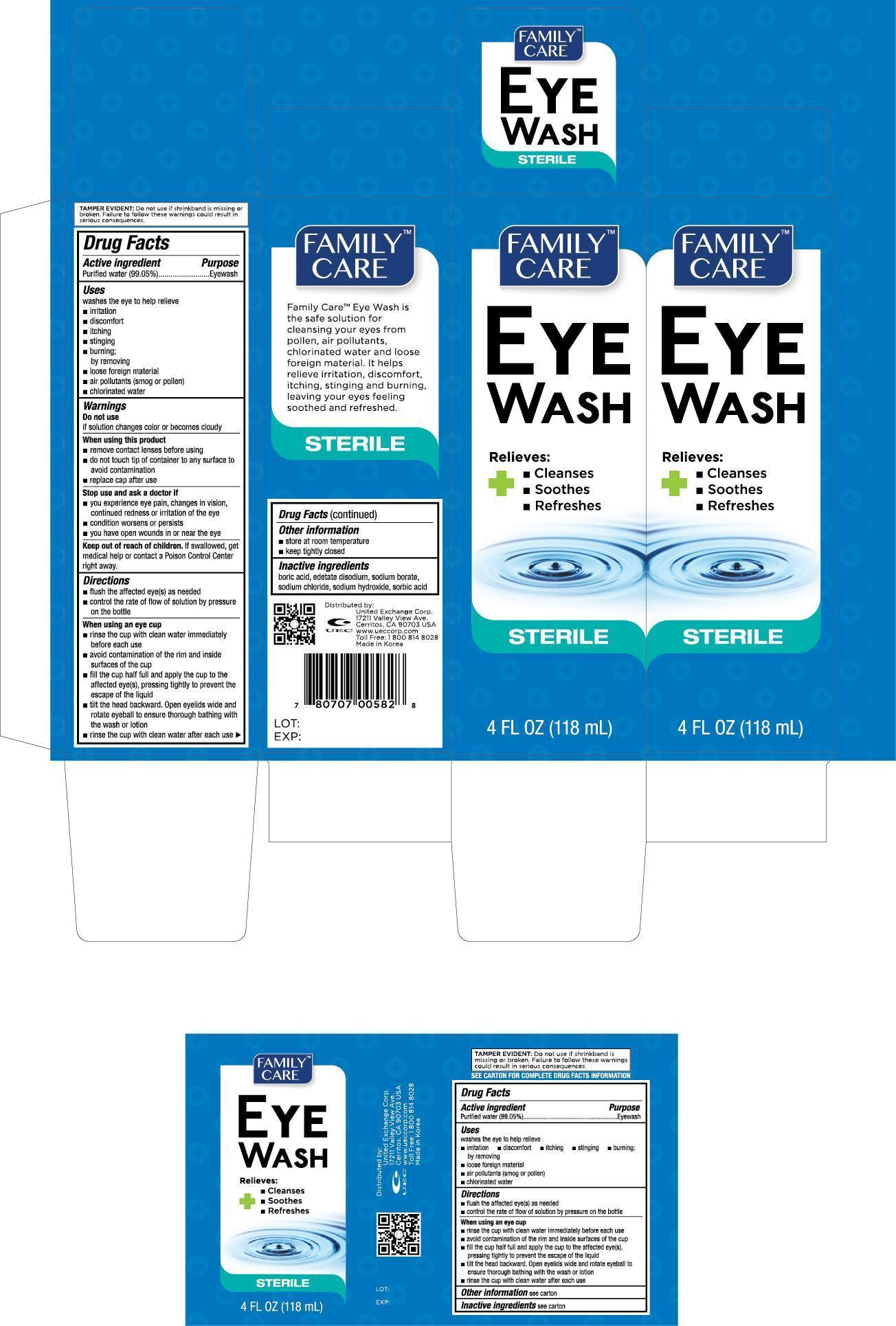 DRUG LABEL: Family Care Eye Wash
NDC: 65923-582 | Form: SOLUTION
Manufacturer: United Exchange Corp.
Category: otc | Type: HUMAN OTC DRUG LABEL
Date: 20150617

ACTIVE INGREDIENTS: WATER 99.05 mL/100 mL
INACTIVE INGREDIENTS: BORIC ACID; EDETATE DISODIUM; SODIUM BORATE; SODIUM CHLORIDE; SODIUM HYDROXIDE; SORBIC ACID

Drug Facts

Active ingredient Purpose

Purified water (99.05%)................................... Eyewash

Uses

washes the eye to help relieve

- irritation
- discomfort
- itching
- stinging
- burning;

by removing

- loose foreign material
- air pollutants (smog or pollen)
- chlorinated water

Warnings

Do not use

if solution changes color or becomes cloudy

When using this product

- remove contact lenses before using
- do not touch tip of container to any surface to avoid contamination
- replace cap after use

Stop use and ask a doctor if

- you experience eye pain, changes in vision, continued redness or irritation of the eye
- condition worsens or persists
- you have open wounds in or near the eye

Keep out of reach of children. If swallowed, get medical help or contact a Poison Control Center right away.

Directions

- flush the affected eye(s) as needed
- control the rate of flow of solution by pressure on the bottle

When using an eye cup

- rinse the cup with clean water immediately before each use
- avoid contamination of the rim and inside surfaces of the cup
- fill the cup half full and apply the cup to the affected eye(s), pressing tightly to prevent the escape of the liquid
- tilt the head backward. Open eyelids wide and rotate eyeball to ensure thorough bathing with the wash or lotion
- rinse the cup with clean water after each use

Other information

- store at room temperature
- keep tightly closed

INACTIVE INGREDIENT

boric acid, edetate disodium, sodium borate, sodium chloride, sodium hydroxide, sodium hydroxide, sorbic acid

DOSAGE AND ADMINISTRATION

Distributed by:

United Exchange Corp.

17211 Valley View Ave.

Cerritos, CA 90703 USA

Made in Korea